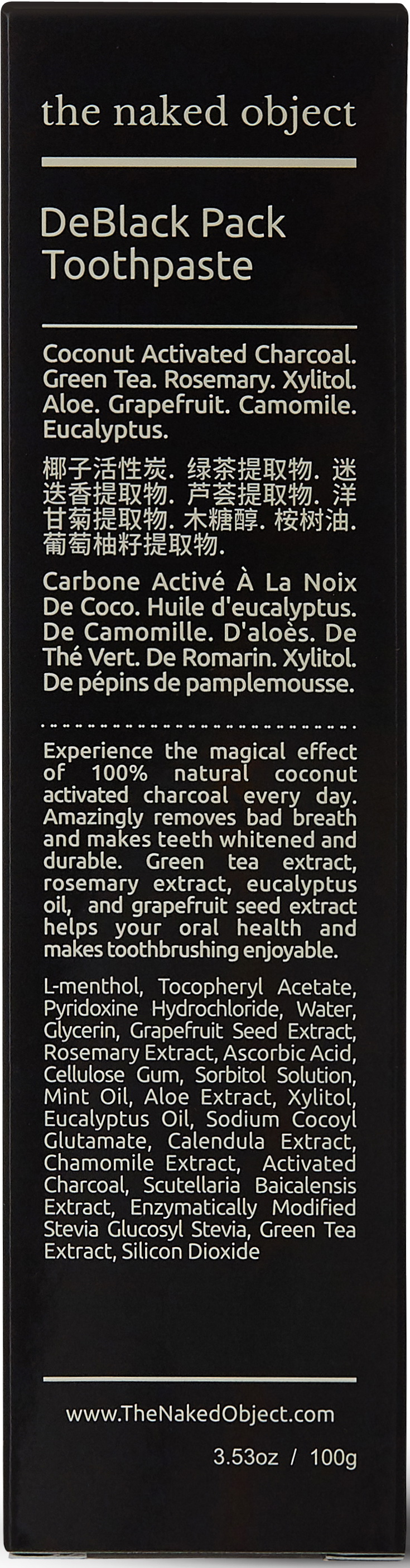 DRUG LABEL: the naked object DeBlack PackToothpaste
NDC: 73112-0001 | Form: PASTE, DENTIFRICE
Manufacturer: JNK Inc
Category: otc | Type: HUMAN OTC DRUG LABEL
Date: 20190510

ACTIVE INGREDIENTS: .ALPHA.-TOCOPHEROL ACETATE 0.1 g/100 g; SILICON DIOXIDE 4 g/100 g
INACTIVE INGREDIENTS: XYLITOL; WATER; ASCORBIC ACID

ACTIVE INGREDIENT

silicon dioxide, tocopherol acetate

PURPOSE

For dental care

Activated Charocal helps removing bad breath, stains, and plaque. Keeps your mouth clean, whiter and firm. Refreshes your mouth and prevents tooth decay, gingivitis, periodontal disease, periodontal disease, gum disease.

Keep out of reach of children

INDICATIONS AND USAGE

A proper amount of toothpaste is put on the toothbrush and the tooth is cleaned by brushing.

Cover your teeth with toothpaste using toothbrush(paste it on teeth). Wait for 1~2minute to let it absorb smell and stains. Afterwards, brush your teeth just like normal toothpaste.

WARNINGS

Storage method

1. Keep it at room temperature in a classified container.

2. Cover and store at room temperature.

3. Store in a not moisture and cool place.

4. Air may come out during use of this product, but there is no problem with its weight.

Usage Precautions

1. Be careful not to swallow. Rinse mouth thoroughly after use

2. If the use of toothpaste causes abnormalities such as gums or mouth injury, discontinue use and consult a doctor or dentist.

3. For children under 6 years of age, use a small amount of toothpaste as small as pea per use, and use under the guidance of a guardian to avoid sucking or swallowing.

4. If a child under 6 years old swallows large amount, consult with a doctor or dentist immediately.

5. Keep out of the reach of children under 6 years of age.

INACTIVE INGREDIENT

Silicon dioxide
Tocopherol acetate
Pyridoxine hydrochloride
glycerin
Sorbitol solution
Cellulose Gum
Ascorbic acid
Sodium cocoyl glutamate
Xylitol
Enzymatically Modified Stevia Glucosyl Stevia
Activated Charcoal/Carbon
Grapefruit Seed Extract
Aloe Extract
Camomile Extract
Greentea Extract
Centella Asiatica Extract
Calendula Extract
Rosemary Extract
L-Menthol
Eucalyptus Oil
Spearmint oil
water

DOSAGE AND ADMINISTRATION

For dental use only